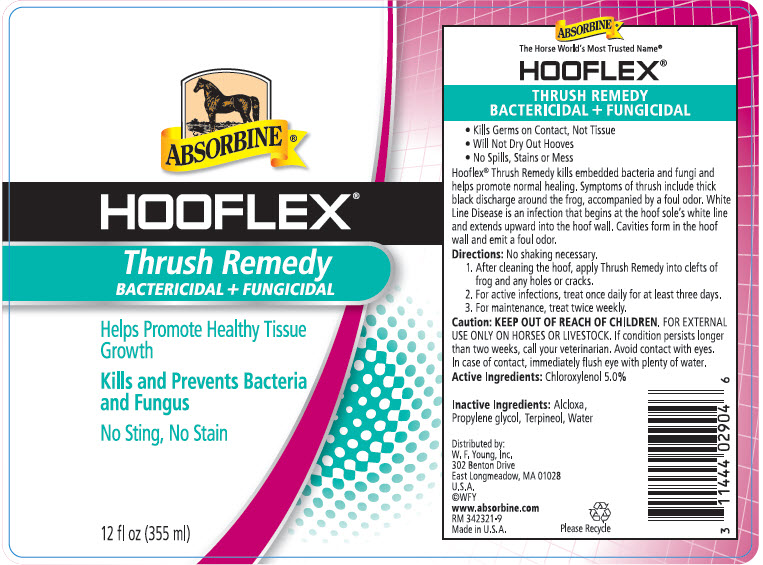 DRUG LABEL: Absorbine Hooflex Thrush Remedy
NDC: 11444-029 | Form: LIQUID
Manufacturer: W. F. Young, Inc.
Category: animal | Type: OTC ANIMAL DRUG LABEL
Date: 20180517

ACTIVE INGREDIENTS: CHLOROXYLENOL 5 g/100 mL

ABSORBINE ®
HOOFLEX®
THRUSH REMEDY
BACTERICIDAL + FUNGICIDAL

VETERINARY INDICATIONS

- Kills Germs on Contact, Not Tissue
- Will Not Dry Out Hooves
- No Spills, Stains or Mess

DESCRIPTION

Hooflex® Thrush Remedy kills embedded bacteria and fungi and helps promote normal healing. Symptoms of thrush include thick black discharge around the frog, accompanied by a foul odor. White Line Disease is an infection that begins at the hoof sole's white line and extends upward into the hoof wall. Cavities form in the hoof wall and emit a foul odor.

Directions

No shaking necessary.

1. After cleaning the hoof, apply Thrush Remedy into clefts of frog and any holes or cracks.
2. For active infections, treat once daily for at least three days.
3. For maintenance, treat twice weekly.

Caution

KEEP OUT OF REACH OF CHILDREN. FOR EXTERNAL USE ONLY ON HORSES OR LIVESTOCK. If condition persists longer than two weeks, call your veterinarian. Avoid contact with eyes. In case of contact, immediately flush eye with plenty of water.

Active Ingredients

Chloroxylenol 5.0%

Inactive Ingredients

Alcloxa, Propylene glycol, Terpineol, Water

Distributed by:
W. F. Young, Inc.
302 Benton Drive
East Longmeadow, MA 01028

PRINCIPAL DISPLAY PANEL - 355 ml Bottle Label

ABSORBINE®

HOOFLEX®

Thrush Remedy
BACTERICIDAL + FUNGICIDAL

Helps Promote Healthy Tissue
Growth

Kills and Prevents Bacteria
and Fungus

No Sting, No Stain

12 fl oz (355 ml)